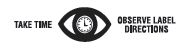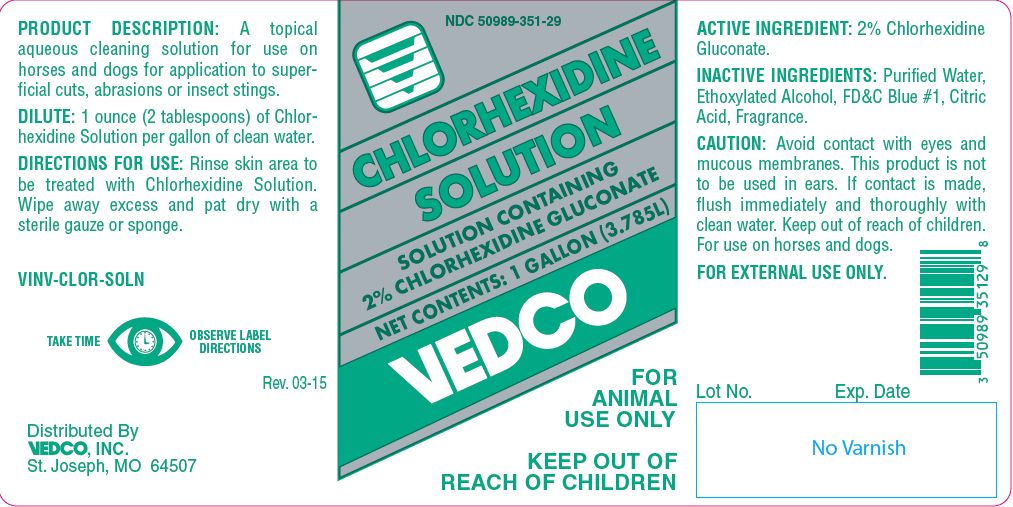 DRUG LABEL: CHLORHEXIDINE
NDC: 50989-351 | Form: SOLUTION
Manufacturer: Vedco, Inc.
Category: animal | Type: OTC ANIMAL DRUG LABEL
Date: 20191011

ACTIVE INGREDIENTS: CHLORHEXIDINE GLUCONATE 99.0 g/1 L

CHLORHEXIDINE SOLUTION
SOLUTION CONTAINING 2% CHLORHEXIDINE GLUCONATE

KEEP OUT OF REACH OF CHILDREN

FOR ANIMAL USE ONLY

KEEP OUT OF REACH OF CHILDREN

PRODUCT DESCRIPTION:

A topical aqueous cleaning solution for use on horses and dogs for application to superficial cuts, abrasions or insect stings.

DILUTE:

1 ounce (2 tablespoons) of Chlorhexidine Solution per gallon of clean water.

DIRECTIONS FOR USE:

Rinse skin area to be treated with Chlorhexidine Solution. Wipe away excess and pat dry with a sterile gauze or sponge.

ACTIVE INGREDIENT:

2% Chlorhexidine Gluconate.

INACTIVE INGREDIENTS:

Purified Water, Ethoxylated Alcohol, FD&C Blue #1, Citric Acid, Fragrance.

CAUTION:

Avoid contact with eyes and mucous membranes. This product is not to be used in ears. If contact is made, flush immediately and thoroughly with clean water. Keep out of reach of children. For use on horses and dogs.
FOR EXTERNAL USE ONLY.

Net Contents:

One Gallon (3.785 L) VINV-CLOR-SOLN

INFORMATION FOR OWNERS/CAREGIVERS

Distributed By

VEDCO, INC.
St. Joseph, MO 64507